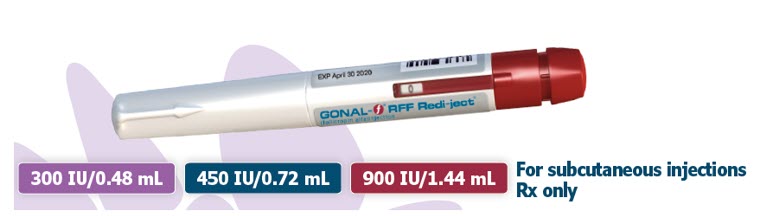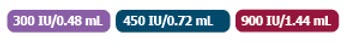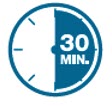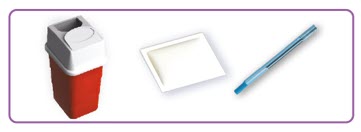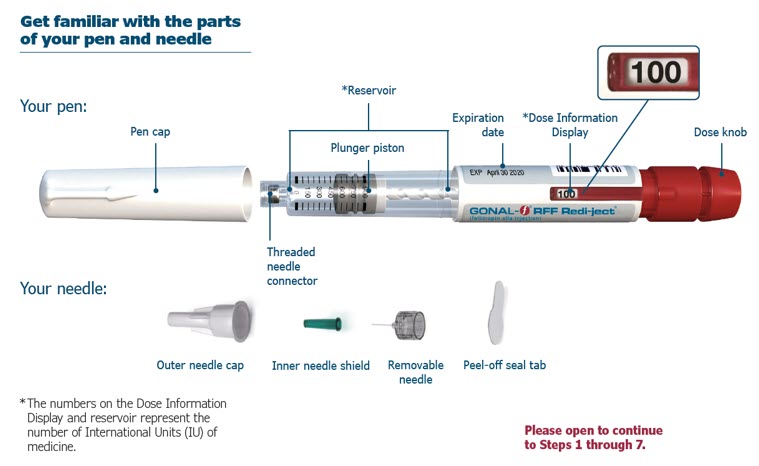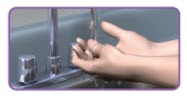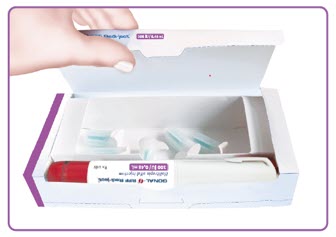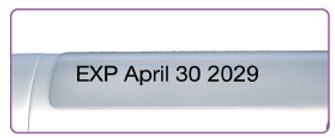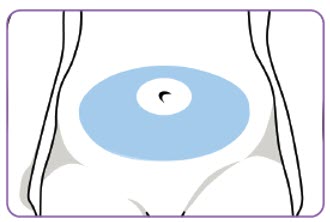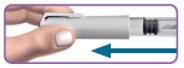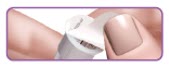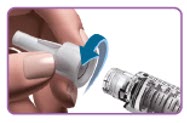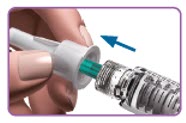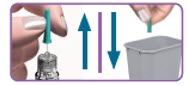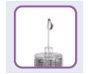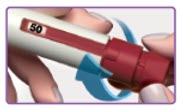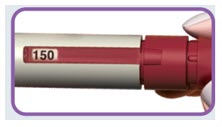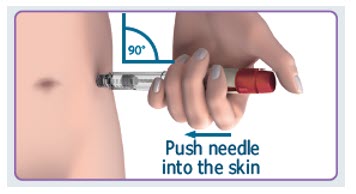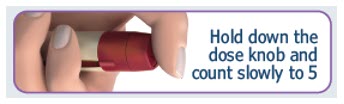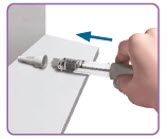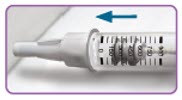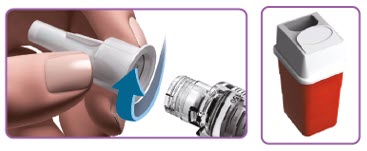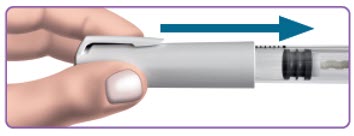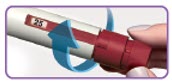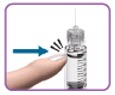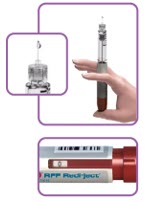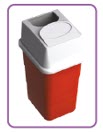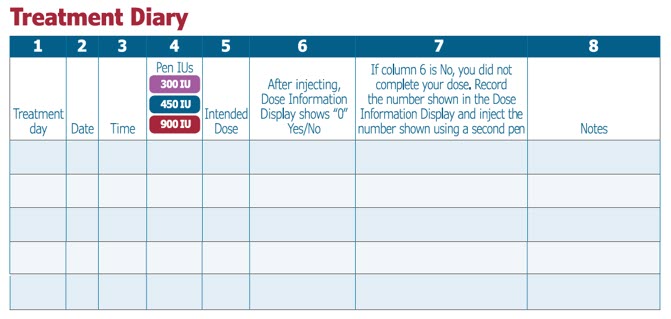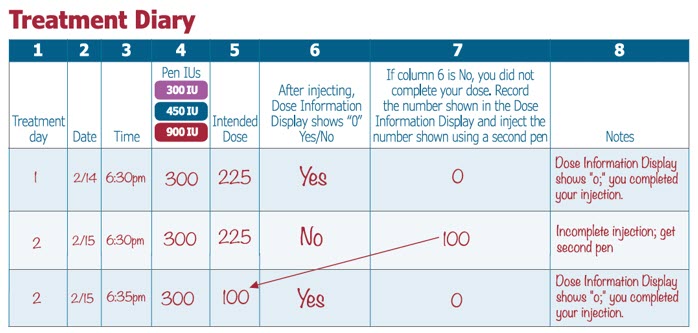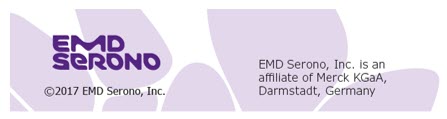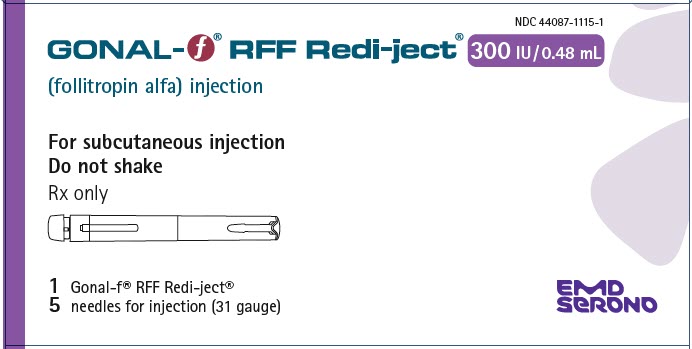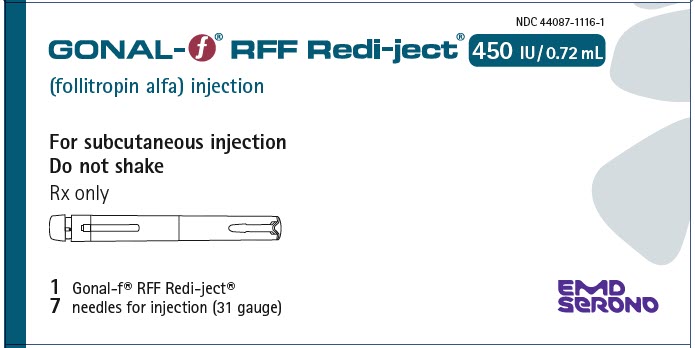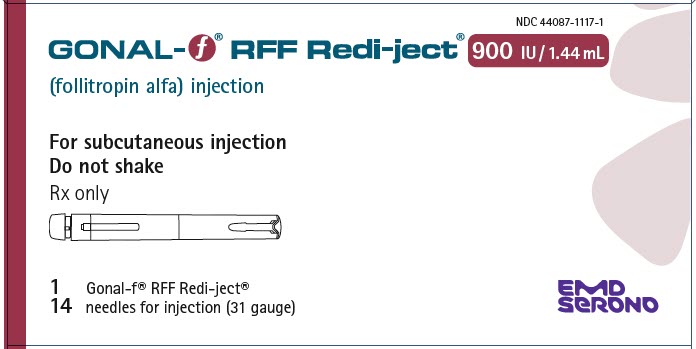 DRUG LABEL: Gonal-f RFF Redi-ject
NDC: 44087-1115 | Form: INJECTION, SOLUTION
Manufacturer: EMD Serono, Inc.
Category: prescription | Type: HUMAN PRESCRIPTION DRUG LABEL
Date: 20250403

ACTIVE INGREDIENTS: FOLLITROPIN 300 [iU]/0.5 mL
INACTIVE INGREDIENTS: SUCROSE; METACRESOL; SODIUM PHOSPHATE, DIBASIC, DIHYDRATE; SODIUM PHOSPHATE, MONOBASIC, MONOHYDRATE; METHIONINE; POLOXAMER 188

HIGHLIGHTS OF PRESCRIBING INFORMATION

These highlights do not include all the information needed to use GONAL-f® RFF Redi-ject® safely and effectively. See full prescribing information for GONAL-f® RFF Redi-ject®
GONAL-f® RFF Redi-ject® (follitropin alfa) injection for subcutaneous use
Initial U.S. Approval: 1997

1 INDICATIONS AND USAGE

GONAL-f® RFF Redi-ject® is a prefilled gonadotropin-containing auto-injection device indicated for:

- Induction of ovulation and pregnancy in oligo-anovulatory women in whom the cause of infertility is functional and not due to primary ovarian failure (1.1)
- Development of multiple follicles in ovulatory women as part of an Assisted Reproductive Technology (ART) cycle (1.2)

2 DOSAGE AND ADMINISTRATION

Ovulation Induction (2.2)

- Initial starting dose of the first cycle - 75 International Units of GONAL-f® RFF Redi-ject® per day for 14 days, administered subcutaneously
- Individualization doses after 14 days
- Doses larger than 300 International Units of FSH per day are not recommended

Assisted Reproductive Technology (2.3)

- Initial starting dose of the first cycle - 150 International Units per day, administered subcutaneously
- Dosage adjustments after 3-5 days and by 75-150 International Units at each adjustment
- Do not administer doses greater than 450 International Units per day

3 DOSAGE FORMS AND STRENGTHS

- Injection: GONAL-f® RFF Redi-ject® 300 International Units per 0.48 mL in prefilled, single-patient-use pen (3)
- Injection: GONAL-f® RFF Redi-ject® 450 International Units per 0.72 mL in prefilled, single-patient-use pen (3)
- Injection: GONAL-f® RFF Redi-ject® 900 International Units per 1.44 mL in prefilled single-patient-use pen (3)

4 CONTRAINDICATIONS

GONAL-f® RFF Redi-ject® is contraindicated in women who exhibit (4):

- Hypersensitivity to recombinant FSH preparations or one of their excipients
- High levels of FSH indicating primary gonadal failure
- Uncontrolled non-gonadal endocrinopathies
- Sex hormone dependent tumors of the reproductive tract and accessory organ.
- Tumors of pituitary gland or hypothalamus
- Abnormal uterine bleeding of undetermined origin
- Ovarian cyst or enlargement of undetermined origin, not due to polycystic ovary syndrome

5 WARNINGS AND PRECAUTIONS

- Hypersensitivity Reactions and Anaphylaxis (5.1)
- Abnormal Ovarian Enlargement (5.2)
- Ovarian Hyperstimulation Syndrome (5.3)
- Pulmonary and Vascular Complications (5.4)
- Ovarian Torsion (5.5)
- Multi-fetal Gestation and Births (5.6)
- Congenital Malformation (5.7)
- Ectopic Pregnancy (5.8)
- Spontaneous Abortion (5.9)
- Ovarian Neoplasms (5.10)

6 ADVERSE REACTIONS

- The most common adverse reactions (≥5%) in ovulation induction include: headache, abdominal pain, ovarian hyperstimulation (6.1)
- The most common adverse reactions (≥5%) in ART include: abdominal pain, nausea, abdominal enlargement, headache, injection site bruising (6.1)

To report SUSPECTED ADVERSE REACTIONS, contact EMD Serono at 1-800-283-8088, Ext 5563 or FDA at 1-800-FDA-1088 or www.fda.gov/medwatch.

8 USE IN SPECIFIC POPULATIONS

- Do not use GONAL-f® RFF Redi-ject® in pregnant women (4, 8.1),
- Nursing Mothers: It is not known whether this drug is excreted in human milk. (8.3)
- Pediatric Use: Safety and efficacy not established. (8.4)
- Renal and Hepatic Insufficiency: Safety, efficacy, and pharmacokinetics of GONAL-f® RFF Redi-ject® in women with renal or hepatic insufficiency have not been established. (8.6)

FULL PRESCRIBING INFORMATION

1 INDICATIONS AND USAGE

1.1 Induction of Ovulation and Pregnancy in Oligo-Anovulatory Women in whom the Cause of Infertility is Functional and Not Due to Primary Ovarian Failure.

Prior to initiation of treatment with GONAL-f® RFF Redi-ject®:

- Perform a complete gynecologic and endocrinologic evaluation
- Exclude primary ovarian failure
- Exclude the possibility of pregnancy
- Demonstrate tubal patency
- Evaluate the fertility status of the male partner

1.2 Development of Multiple Follicles in Ovulatory Women as Part of an Assisted Reproductive Technology (ART) Cycle.

Prior to initiation of treatment with GONAL-f® RFF Redi-ject®:

- Perform a complete gynecologic and endocrinologic evaluation, and diagnose the cause of infertility
- Exclude the possibility of pregnancy
- Evaluate the fertility status of the male partner

2 DOSAGE AND ADMINISTRATION

2.1 General Dosing Information

- Parenteral drug products should be inspected visually for particulate matter and discoloration prior to administration, whenever solution and container permit.
- GONAL-f® RFF Redi-ject® is a pre-filled disposable auto-injection device intended for multiple dose use.
- GONAL-f® RFF Redi-ject® can be set in 12.5 International Units increments.
- Administer GONAL-f® RFF Redi-ject® subcutaneously in the abdomen as described in Instructions for Use
- Do not attempt to mix any other medications inside of the device with GONAL-f® RFF Redi-ject®.
- Instruct women to remove the GONAL-f® RFF Redi-ject® from the refrigerator at least 30 minutes prior to use in order to allow GONAL-f® RFF Redi-ject® to warm to room temperature and avoid the discomfort of a cold injection.

2.2 Recommended Dosing for Ovulation Induction

The dosing scheme is stepwise and is individualized for each woman [see Clinical Studies (14.1)]. Starting doses less than 37.5 International Units have not been studied in clinical trials and are not recommended.

- A starting daily dose of 75 International Units of GONAL-f® RFF Redi-ject® is administered subcutaneously daily for 14 days in the first cycle of use.
  In subsequent cycles of treatment, the starting dose (and dosage adjustments) of GONAL-f® RFF Redi-ject® should be determined based on the history of the ovarian response to GONAL-f® RFF Redi-ject®.
- The following should be considered when planning the woman's individualized dose:
  - Appropriate GONAL-f® RFF Redi-ject® dose adjustment(s) should be used to prevent multiple follicular growth and cycle cancellation.
  - The maximum, individualized, daily dose of GONAL-f® RFF Redi-ject® is 300 International Units per day.
  - In general, do not exceed 35 days of treatment.
- If indicated by the ovarian response after the initial 14 days, make an incremental adjustment in dose, up to 37.5 International Units.
- If indicated by the ovarian response, make additional adjustments in dose, up to 37.5 International Units, every 7 days.
- Treatment should continue until follicular growth and/or serum estradiol levels indicate an adequate ovarian response.
- When pre-ovulatory conditions are reached, administer human chorionic gonadotropin (hCG) to induce final oocyte maturation and ovulation.
  Withhold hCG in cases where the ovarian monitoring suggests an increased risk of ovarian hyperstimulation syndrome (OHSS) on the last day of GONAL-f® RFF Redi-ject® therapy [see Warnings and Precautions (5.2, 5.3, 5.11)].
- Encourage the woman and her partner to have intercourse daily, beginning on the day prior to the administration of hCG and until ovulation becomes apparent.
  Discourage intercourse when the risk for OHSS is increased [see Warnings and Precautions (5.2, 5.3)].

2.3 Recommended Dosing for Assisted Reproductive Technology

The dosing scheme follows a stepwise approach and is individualized for each woman.

- Beginning on cycle day 2 or 3, a starting dose of 150 International Units of GONAL-f® RFF Redi-ject® is administered subcutaneously daily until sufficient follicular development, as determined by ultrasound in combination with measurement of serum estradiol levels, is attained. In most cases, therapy should not exceed 10 days.
  In women under 35 years of age whose endogenous gonadotropin levels are suppressed, initiate GONAL-f® RFF Redi-ject® administration at a dose of 150 International Units per day.
  In women 35 years of age and older whose endogenous gonadotropin levels are suppressed, initiate GONAL-f® RFF Redi-ject® administration at a dose of 225 International Units per day.
- Adjust the dose after 5 days based on the woman's ovarian response, as determined by ultrasound evaluation of follicular growth and serum estradiol levels.
- Do not make additional dosage adjustments more frequently than every 3-5 days or by more than 75-150 International Units at each adjustment.
- Continue treatment until adequate follicular development is evident, and then administer hCG.
  The administration of hCG should be withheld in cases where the ovarian monitoring suggests an increased risk of OHSS on the last day of GONAL-f® RFF Redi-ject® therapy [see Warnings and Precautions (5.2, 5.3, 5.11)].
- Doses greater than 450 International Units per day are not recommended.

3 DOSAGE FORMS AND STRENGTHS

GONAL-f® RFF Redi-ject is a clear and colorless to slightly yellow solution available as:

• Injection: | GONAL-f® RFF Redi-ject® 300 International Units per 0.48 mL in prefilled, single-patient-use pen
• Injection: | GONAL-f® RFF Redi-ject® 450 International Units per 0.72 mL in prefilled, single-patient-use pen
• Injection: | GONAL-f® RFF Redi-ject® 900 International Units per 1.44 mL in prefilled, single-patient-use pen

4 CONTRAINDICATIONS

GONAL-f® RFF Redi-ject® is contraindicated in women who exhibit:

- Prior hypersensitivity to recombinant FSH products
- High levels of FSH indicating primary gonadal failure
- Presence of uncontrolled non-gonadal endocrinopathies (e.g., thyroid, adrenal, or pituitary disorders) [see Indications and Usage (1.1, 1.2)]
- Sex hormone dependent tumors of the reproductive tract and accessory organs
- Tumors of pituitary gland or hypothalamus
- Abnormal uterine bleeding of undetermined origin
- Ovarian cyst or enlargement of undetermined origin, not due to polycystic ovary syndrome

5 WARNINGS AND PRECAUTIONS

GONAL-f® RFF Redi-ject® should only be used by physicians who are experienced in infertility treatment. GONAL-f® RFF Redi-ject® contains a gonadotropic substance capable of causing Ovarian Hyperstimulation Syndrome (OHSS) in women with or without pulmonary or vascular complications [see Warnings and Precautions (5.2, 5.3, 5.4, 5.5)] and multiple births [see Warnings and Precautions (5.6)]. Gonadotropin therapy requires the availability of appropriate monitoring facilities [see Warnings and Precautions (5.11)]. The lowest effective dose should be used.

Careful attention should be given to the diagnosis of infertility and the selection of candidates for GONAL-f® RFF Redi-ject® therapy [see Indications and Usage (1.1, 1.2) and Dosage and Administration (2.2, 2.3)].

5.1 Hypersensitivity Reactions and Anaphylaxis

Serious systemic hypersensitivity reactions, including anaphylaxis, have been reported in the postmarketing experience with GONAL-f® and GONAL-f® RFF. Symptoms have included dyspnea, facial edema, pruritus, and urticaria. If an anaphylactic or other serious allergic reaction occurs, initiate appropriate therapy including supportive measures if cardiovascular instability and/or respiratory compromise occur, and discontinue further use.

5.2 Abnormal Ovarian Enlargement

In order to minimize the hazards associated with abnormal ovarian enlargement that may occur with GONAL-f® RFF Redi-ject® therapy, treatment should be individualized and the lowest effective dose should be used [see Dosage and Administration (2.2, 2.3)]. Use of ultrasound monitoring of ovarian response and/or measurement of serum estradiol levels is important to minimize the risk of ovarian stimulation [see Warnings and Precautions (5.11)].

If the ovaries are abnormally enlarged on the last day of GONAL-f® RFF Redi-ject® therapy, hCG should not be administered in order to reduce the chance of developing Ovarian Hyperstimulation Syndrome (OHSS) [see Warnings and Precautions (5.3)]. Intercourse should be prohibited in women with significant ovarian enlargement after ovulation because of the danger of hemoperitoneum resulting from rupture of ovarian cysts [see Warnings and Precautions (5.3)].

5.3 Ovarian Hyperstimulation Syndrome (OHSS)

OHSS is a medical entity distinct from uncomplicated ovarian enlargement and may progress rapidly to become a serious medical event. OHSS is characterized by a dramatic increase in vascular permeability, which can result in a rapid accumulation of fluid in the peritoneal cavity, thorax, and potentially, the pericardium. The early warning signs of development of OHSS are severe pelvic pain, nausea, vomiting, and weight gain. Abdominal pain, abdominal distension, gastrointestinal symptoms including nausea, vomiting and diarrhea, severe ovarian enlargement, weight gain, dyspnea, and oliguria have been reported with OHSS. Clinical evaluation may reveal hypovolemia, hemoconcentration, electrolyte imbalances, ascites, hemoperitoneum, pleural effusions, hydrothorax, acute pulmonary distress, and thromboembolic reactions [see Warnings and Precautions (5.4)]. Transient liver function test abnormalities suggestive of hepatic dysfunction with or without morphologic changes on liver biopsy, have been reported in association with OHSS.

OHSS occurs after gonadotropin treatment has been discontinued and it can develop rapidly, reaching its maximum about seven to ten days following treatment. Usually, OHSS resolves spontaneously with the onset of menses. If there is evidence that OHSS may be developing prior to hCG administration [see Warnings and Precautions (5.2)], the hCG must be withheld. Cases of OHSS are more common, more severe, and more protracted if pregnancy occurs; therefore, women should be assessed for the development of OHSS for at least two weeks after hCG administration.

If serious OHSS occurs, gonadotropins, including hCG, should be stopped and consideration should be given as to whether the woman needs to be hospitalized. Treatment is primarily symptomatic and overall should consist of bed rest, fluid and electrolyte management, and analgesics (if needed). Because the use of diuretics can accentuate the diminished intravascular volume, diuretics should be avoided except in the late phase of resolution as described below. The management of OHSS may be divided into three phases as follows:

- Acute Phase:
  Management should be directed at preventing hemoconcentration due to loss of intravascular volume to the third space and minimizing the risk of thromboembolic phenomena and kidney damage. Fluid intake and output, weight, hematocrit, serum and urinary electrolytes, urine specific gravity, BUN and creatinine, total proteins with albumin: globulin ratio, coagulation studies, electrocardiogram to monitor for hyperkalemia, and abdominal girth should be thoroughly assessed daily or more often based on the clinical need. Treatment, consisting of limited intravenous fluids, electrolytes, human serum albumin, is intended to normalize electrolytes while maintaining an acceptable but somewhat reduced intravascular volume. Full correction of the intravascular volume deficit may lead to an unacceptable increase in the amount of third space fluid accumulation.
- Chronic Phase:
  After the acute phase is successfully managed as above, excessive fluid accumulation in the third space should be limited by instituting severe potassium, sodium, and fluid restriction.
- Resolution Phase:
  As third space fluid returns to the intravascular compartment, a fall in hematocrit and increasing urinary output are observed in the absence of any increase in intake. Peripheral and/or pulmonary edema may result if the kidneys are unable to excrete third space fluid as rapidly as it is mobilized. Diuretics may be indicated during the resolution phase, if necessary, to combat pulmonary edema.

Ascitic, pleural, and pericardial fluid should not be removed unless there is the necessity to relieve symptoms such as pulmonary distress or cardiac tamponade.

OHSS increases the risk of injury to the ovary. Pelvic examination or intercourse may cause rupture of an ovarian cyst, which may result in hemoperitoneum, and should therefore be avoided.

If bleeding occurs and requires surgical intervention, the clinical objective should be to control the bleeding and retain as much ovarian tissue as possible. A physician experienced in the management of this syndrome, or who is experienced in the management of fluid and electrolyte imbalances should be consulted.

During clinical trials with GONAL-f® RFF, OHSS occurred in 7.2% of 83 women and 4.6% of 237 women treated with GONAL-f® RFF for ovulation induction and during Assisted Reproductive Technology, respectively.

5.4 Pulmonary and Vascular Complications

Serious pulmonary conditions (e.g., atelectasis, acute respiratory distress syndrome and exacerbation of asthma) have been reported in women treated with gonadotropins. In addition, thromboembolic events both in association with, and separate from OHSS have been reported in women treated with gonadotropins including GONAL-f® RFF. Intravascular thrombosis and embolism, which may originate in venous or arterial vessels, can result in reduced blood flow to critical organs or the extremities. Women with generally recognized risk factors for thrombosis, such as personal or family history, severe obesity, or thrombophilia, may have an increased risk of venous or arterial thromboembolic events, during or following treatment with gonadotropins. Sequelae of such reactions have included venous thrombophlebitis, pulmonary embolism, pulmonary infarction, cerebral vascular occlusion (stroke), and arterial occlusion resulting in loss of limb and rarely in myocardial infarctions. In rare cases, pulmonary complications and/or thromboembolic reactions have resulted in death. In women with recognized risk factors, the benefits of ovulation induction and assisted reproductive technology need to be weighed against the risks. It should be noted that pregnancy also carries an increased risk of thrombosis.

5.5 Ovarian Torsion

Ovarian torsion has been reported after treatment with gonadotropins. This may be related to OHSS, pregnancy, previous abdominal surgery, past history of ovarian torsion, previous or current ovarian cyst and polycystic ovaries. Damage to the ovary due to reduced blood supply can be limited by early diagnosis and immediate detorsion.

5.6 Multi-fetal Gestation and Birth

Multi-fetal gestation and births have been reported with all gonadotropin therapy including therapy with GONAL-f® RFF.

During clinical trials with GONAL-f® RFF, multiple births occurred in 20% of live births in women receiving therapy for ovulation induction and 35.1 % of live births in women undergoing ART.

The woman and her partner should be advised of the potential risk of multi-fetal gestation and birth before beginning therapy with GONAL-f® RFF Redi-ject®.

5.7 Congenital Malformations

The incidence of congenital malformations after some ART [specifically in vitro fertilization (IVF) or intracytoplasmic sperm injection (ICSI)] may be slightly higher than after spontaneous conception. This slightly higher incidence is thought to be related to differences in parental characteristics (e.g., maternal age, maternal and paternal genetic background, sperm characteristics) and to the higher incidence of multi-fetal gestations after IVF or ICSI. There are no indications that the use of gonadotropins during IVF or ICSI is associated with an increased risk of congenital malformations.

5.8 Ectopic Pregnancy

Since infertile women undergoing ART often have tubal abnormalities, the incidence of ectopic pregnancy may be increased. Early confirmation of intrauterine pregnancy should be determined by β-hCG testing and transvaginal ultrasound.

5.9 Spontaneous Abortion

The risk of spontaneous abortion (miscarriage) is increased with gonadotropin products. However, causality has not been established. The increased risk may be a factor of the underlying infertility.

5.10 Ovarian Neoplasms

There have been infrequent reports of ovarian neoplasms, both benign and malignant, in women who have had multiple drug therapy for controlled ovarian stimulation, however, a causal relationship has not been established.

5.11 Laboratory Tests

In most instances, treatment of women with GONAL-f® RFF Redi-ject® will result only in follicular growth and maturation. In the absence of an endogenous LH surge, hCG is given when monitoring of the woman indicates that sufficient follicular development has occurred. This may be estimated by ultrasound alone or in combination with measurement of serum estradiol levels. The combination of both ultrasound and serum estradiol measurement are useful for monitoring follicular growth and maturation, timing of the ovulatory trigger, detecting ovarian enlargement and minimizing the risk of the OHSS and multiple gestation.

The clinical confirmation of ovulation is obtained by direct or indirect indices of progesterone production as well as sonographic evidence of ovulation.

Direct or indirect indices of progesterone production:

- Urinary or serum luteinizing hormone (LH) rise
- A rise in basal body temperature
- Increase in serum progesterone
- Menstruation following a shift in basal body temperature

Sonographic evidence of ovulation:

- Collapsed follicle
- Fluid in the cul-de-sac
- Features consistent with corpus luteum formation
- Secretory endometrium

6 ADVERSE REACTIONS

The following serious adverse reactions are discussed elsewhere in the labeling:

- Hypersensitivity Reactions and Anaphylaxis [see Warnings and Precautions (5.1)]
- Abnormal Ovarian Enlargement [see Warnings and Precautions (5.2)]
- Ovarian Hyperstimulation Syndrome [see Warnings and Precautions (5.3)]
- Atelectasis, acute respiratory distress syndrome and exacerbation of asthma [see Warnings and Precautions (5.4)]
- Thromboembolic events [see Warnings and Precautions (5.4)]
- Ovarian Torsion [see Warnings and Precautions (5.5)]
- Multi-fetal Gestation and Birth [see Warnings and Precautions (5.6)]
- Congenital Malformations [see Warnings and Precautions (5.7)]
- Ectopic Pregnancy [see Warnings and Precautions (5.8)]
- Spontaneous Abortion [see Warnings and Precautions (5.9)]
- Ovarian Neoplasms [see Warnings and Precautions (5.10)]

6.1 Clinical Study Experience

Because clinical trials are conducted under widely varying conditions, adverse reaction rates observed in the clinical trials of a drug cannot be directly compared to rates in the clinical trial of another drug and may not reflect the rates observed in practice.

The safety of GONAL-f® RFF was examined in two clinical studies (one ovulation induction study and one ART study).

Ovulation Induction

In a multiple cycle (3), assessor-blind, multinational, multicenter, active comparator study vs. a recombinant FSH comparator, a total of 83 oligo-anovulatory infertile women were randomized and underwent ovulation induction with GONAL-f® RFF. Adverse reactions occurring in at least 2.0% of women receiving GONAL-f® RFF are listed in Table 1.

Table 1: Common Adverse Reactions Reported at a Frequency of ≥ 2% in an Ovulation Induction Study
System Organ Class/Adverse Reactions | GONAL-f® RFF N=83 [total number of women treated with GONAL-f® RFF] (176 treatment cycles [up to 3 treatment cycles per woman]) n [number of women with the adverse reaction] (%)
Central and Peripheral Nervous System
Headache | 22 (26.5%)
Gastrointestinal System
Abdominal Pain | 10 (12.0%)
Nausea | 3 (3.6%)
Flatulence | 3 (3.6%)
Diarrhea | 3 (3.6%)
Neoplasm
Ovarian Cyst | 3 (3.6%)
Reproductive, Female
Ovarian Hyperstimulation | 6 (7.2%)
Application Site
Injection Site Pain | 4 (4.8%)
Injection Site Inflammation | 2 (2.4%)

Assisted Reproductive Technology

In a single cycle, assessor-blind, multinational, multicenter, active comparator study vs. a recombinant FSH comparator, a total of 237 normal ovulatory infertile women were randomized and received GONAL-f® RFF as part of an ART [in vitro fertilization (IVF) or intracytoplasmic sperm injection cycle (ICSI)] cycle. All women received pituitary down-regulation with gonadotropin releasing hormone (GnRH) agonist before stimulation. Adverse Reactions occurring in at least 2.0% of women are listed in Table 2.

Table 2: Common Adverse Reactions Reported at a Frequency of ≥ 2% in an Assisted Reproductive Technologies Study
System Organ Class/Adverse Reactions | GONAL-f® RFF N=237 [total number of women treated with GONAL-f® RFF] n [number of women with the adverse reaction] (%)
Gastrointestinal System
Abdominal Pain | 55 (23.2%)
Nausea | 19 (8.0%)
Body as a Whole- General
Abdomen Enlarged | 33 (13.9%)
Central and Peripheral Nervous System
Headache | 44 (18.6%)
Application Site Disorders
Injection Site Bruising | 23 (9.7%)
Injection Site Pain | 13 (5.5%)
Injection Site Inflammation | 10 (4.2%)
Injection Site Reaction | 10 (4.2%)
Application Site Edema | 6 (2.5%)
Reproductive, Female
Ovarian Hyperstimulation | 11 (4.6%)

6.2 Postmarketing Experience

The following adverse reactions have been reported during postmarketing use of GONAL-f® RFF. Because these reactions were reported voluntarily from a population of uncertain size, the frequency or a causal relationship to GONAL^-f® RFF cannot be reliably determined.

Body as a Whole - General: hypersensitivity reactions including anaphylactoid reactions [see Warnings and Precautions (5.1)]

Respiratory System: asthma

Vascular disorders: thromboembolism [see Warnings and Precautions (5.4)]

7 DRUG INTERACTIONS

No drug-drug interaction studies have been performed.

8 USE IN SPECIFIC POPULATIONS

8.1 Pregnancy

Risk Summary

GONAL-f® RFF Redi-ject® is not indicated in pregnant women.

The incidence of congenital malformations after some Assisted Reproductive Technology (ART), procedures, specifically in vitro fertilization (IVF) or intracytoplasmic sperm injection (ICSI)], may be slightly higher than after spontaneous conception. This slightly higher incidence is thought to be related to differences in parental characteristics (e.g., maternal age, maternal and paternal genetic background, sperm characteristics) and to a higher incidence of multi-fetal gestations after IVF or ICSI. There is no human data that the use of gonadotropins (including GONAL-f® RFF Redi-ject®), alone or as part of IVF or ICSI cycles, increases the risk of congenital malformations.

The risk of spontaneous abortion (miscarriage) is increased in women who have used gonadotropins products (including GONAL-f® RFF Redi-ject®) to achieve pregnancy.

In animal studies, the continuous administration of recombinant human FSH during pregnancy resulted in a decrease in the number of viable fetuses and difficult and prolonged delivery. No teratogenic effect has been observed.

In the US general population, the estimated background risk of major birth defects and miscarriage after spontaneous clinically recognized pregnancies, is 2% to 4% and 15% to 20%, respectively.

Data

Human Data

Data on a limited number of exposed pregnancies indicate no adverse reactions of gonadotropins on pregnancy, embryonal or fetal development, parturition or postnatal development following controlled ovarian stimulation.

Animal Data

Embryofetal development studies with recombinant human FSH in rats, where dosing occurred during organogenesis, showed a dose dependent increase in difficult and prolonged parturition in dams, and dose dependent increases in resorptions, pre- and post-implantation losses, and stillborn pups at doses representing 5 and 41 times the lowest clinical dose of 75 IU based on body surface area. Pre-/post-natal development studies with recombinant human FSH in rats, where dosing occurred from mid-gestation through lactation, showed difficult and prolonged parturition in all dams dosed at 41 times the lowest clinical dose of 75 IU based on body surface area, along with maternal death and stillborn pups associated with the difficult and prolonged parturition. This toxicity was not observed in dams and offspring dosed at a level 5 times the lowest clinical dose of 75 IU based on body surface area.

8.2 Lactation

There are no data on the presence of GONAL-F RFF in human milk, the effects on the breastfed infant, or the effects on milk production. Because the secretion of prolactin during lactation can result in inadequate response to ovarian stimulation, advise women not to breast feed during treatment with GONAL-f® RFF Redi-ject®.

8.3 Females and Males of Reproductive Potential

Since GONAL-f® RFF Redi-ject® is not indicated in pregnant women, verify a negative pregnancy test before administering GONAL-f® RFF Redi-ject® to a woman [see Dosage and Administration (2.2, 2.3)].

8.4 Pediatric Use

Safety and effectiveness in pediatric patients have not been established.

8.6 Renal and Hepatic Insufficiency

Safety, efficacy, and pharmacokinetics of GONAL-f® RFF Redi-ject® in women with renal or hepatic insufficiency have not been established.

10 OVERDOSAGE

Aside from possible OHSS [see Warnings and Precautions (5.3)] and multiple gestations [see Warnings and Precautions (5.6)], there is no additional information on the consequences of acute overdosage with GONAL-f® RFF Redi-ject®.

11 DESCRIPTION

Follitropin alfa, a gonadotropin [human follicle stimulating hormone (hFSH)], is a glycoprotein hormone produced by recombinant DNA technology in a Chinese Hamster Ovary (CHO) cell line. It has a dimeric structure consisting of two glycoprotein subunits (alpha and beta). The alpha and beta subunits have 92 and 111 amino acids, respectively, and their primary and tertiary structures are indistinguishable from those of human follicle stimulating hormone. The molecular weight is approximately 31 kDa (14 kDa for alpha subunit and 17 kDa for beta subunit).

GONAL-f® RFF Redi-ject® (follitropin alfa) injection is a sterile, clear and colorless to slightly yellow solution in disposable, prefilled single-patient-use pen intended for the subcutaneous use.

Each GONAL-f® RFF Redi-ject® pen delivers 300 International Units (22 mcg) follitropin alfa in 0.48 mL and the inactive ingredients: dibasic sodium phosphate (0.43 mg), m-cresol (1.47 mg), methionine (0.05 mg), monobasic sodium phosphate (0.19 mg), poloxamer (0.05 mg), sucrose (29.47 mg) and Water for Injection USP. Phosphoric acid and/or sodium hydroxide may be used to adjust the pH to 7.

Each GONAL-f® RFF Redi-ject® pen delivers 450 International Units (33 mcg) follitropin alfa in 0.72 mL and the inactive ingredients: dibasic sodium phosphate (0.65 mg), m-cresol (2.21 mg), methionine (0.07 mg), monobasic sodium phosphate (0.29 mg), poloxamer (0.07 mg), sucrose (44.20 mg) and Water for Injection USP. Phosphoric acid and/or sodium hydroxide may be used to adjust the pH to 7.

Each GONAL-f® RFF Redi-ject® pen delivers 900 International Units (66 mcg) follitropin alfa in 1.44 mL and the inactive ingredients: dibasic sodium phosphate (1.3 mg), m-cresol (4.42 mg), methionine (0.15 mg), monobasic sodium phosphate (0.58 mg), poloxamer (0.15 mg), sucrose (88.41 mg) and Water for Injection USP. Phosphoric acid and/or sodium hydroxide may be used to adjust the pH to 7.

Under current storage conditions, GONAL-f® RFF Redi-ject® may contain up to 10% of oxidized follitropin alfa.

12 CLINICAL PHARMACOLOGY

12.1 Mechanism of Action

Follicle stimulating hormone (FSH), the active component in GONAL-f® RFF Redi-ject®, is required for normal follicular growth, follicular maturation, and gonadal steroid production. The level of FSH is critical for the onset and duration of follicular development, and consequently for the timing and number of follicles reaching maturity.

GONAL-f® RFF Redi-ject® stimulates ovarian follicular growth in women who do not have primary ovarian failure. In order to effect the final phase of follicle maturation, resumption of meiosis, and rupture of the follicle in the absence of an endogenous LH surge, human chorionic gonadotropin (hCG) must be given following treatment with GONAL-f® RFF Redi-ject® when monitoring of the woman indicates that appropriate follicular development parameters have been achieved. There is inter-woman variability in response to FSH administration.

12.3 Pharmacokinetics

Single-dose pharmacokinetics of follitropin alfa were determined following subcutaneous administration of 300 International Units of GONAL-f® RFF Redi-ject® to 21 pre-menopausal healthy female volunteers who were pituitary down-regulated with a GnRH agonist.

The descriptive statistics for the pharmacokinetic parameters are presented in Table 3.

Table 3: Pharmacokinetic parameters of FSH following administration of GONAL-f® RFF Redi-ject® (300 International Units subcutaneously in a single dose)
Parameter |  | Healthy Volunteers (N=21)
 |  |  | Mean |  | % CV
 | AUClast (IU hr/L) |  | 884 |  | 20%
 | Cmax (IU/L) |  | 9.83 |  | 23%
 | tmax (hr) |  | 15.5 |  | 43%
 | t1/2 (hr) |  | 53 |  | 52%
Abbreviations are:
Cmax: peak concentration (above baseline)
tmax: time of Cmax
t1/2: elimination half life

Absorption

The absorption rate of GONAL-f® RFF Redi-ject® following subcutaneous administration is slower than the elimination rate. Hence, the pharmacokinetics of GONAL-f® RFF Redi-ject® are absorption rate-limited.

Distribution

Human tissue or organ distribution of FSH has not been determined for GONAL-f® RFF Redi-ject®.

Metabolism/Excretion

FSH metabolism and excretion following administration of GONAL-f® RFF Redi-ject® have not been studied in humans.

13 NONCLINICAL TOXICOLOGY

13.1 Carcinogenesis, Mutagenesis, Impairment of Fertility

Long-term studies in animals have not been performed to evaluate the carcinogenic potential of GONAL-f® RFF Redi-ject®. However, follitropin alfa showed no mutagenic activity in a series of tests performed to evaluate its potential genetic toxicity including, bacterial and mammalian cell mutation tests, a chromosomal aberration test and a micronucleus test.

Impaired fertility has been reported in rats, exposed to pharmacological doses of follitropin alfa (greater than or equal to 40 International Units per kg per day, greater than or equal to 5 times the lowest clinical dose of 75 International Units) for extended periods, through reduced fecundity.

14 CLINICAL STUDIES

The safety and efficacy of GONAL-f® RFF were examined in two clinical studies (one ovulation induction study and one ART study).

14.1 Ovulation Induction (OI)

Ovulation induction was evaluated in a randomized, assessor-blind, multinational, multicenter, active-controlled, study in oligo-anovulatory infertile women. Women were randomized to either GONAL-f® RFF (n=83), administered subcutaneously, or a comparator recombinant human FSH. The use of insulin-sensitizing agents was allowed during the study. The study was designed to evaluate and compare mean ovulation rates in the first cycle of treatment. Results for GONAL-f® RFF are presented in Table 4. Also presented in this table are secondary outcome results from cycle 1 through cycle 3. The study was not powered to demonstrate differences in any of the secondary outcomes.

Table 4: Cumulative Ovulation and Clinical Pregnancy Rates in Ovulation Induction
Cycle | GONAL-f® RFF (n=83)
Cycle | Cumulative [Cumulative rates were determined per woman over cycles 1, 2, and 3.] Percent Ovulation |  | Cumulative Clinical Pregnancy [Clinical pregnancy was defined as a pregnancy for which a fetal sac (with or without heart activity) was visualized by ultrasound on day 34-36 after hCG administration.] Rate
Cycle 1 |  | 72% [Non-inferior to comparator recombinant human FSH based on a two-sided 95% confidence interval, intent-to-treat analysis.] |  | 28% [Secondary efficacy outcomes. The study was not powered to demonstrate differences in these outcomes.]
Cycle 2 |  | 89% |  | 41%
Cycle 3 |  | 92% |  | 45%

14.2 Assisted Reproductive Technology (ART)

The efficacy of GONAL-f® RFF was evaluated in a randomized, assessor-blind, multinational, multicenter, active controlled study in healthy normal ovulatory, infertile women treated for one cycle with controlled ovarian stimulation, as part of an ART [in vitro fertilization (IVF), or intracytoplasmic sperm injection (ICSI)] cycle. Women were randomized to either GONAL-f® RFF (n=237), administered subcutaneously, or a comparator recombinant human FSH. Randomization was stratified by insemination technique, (IVF vs. ICSI). All women received pituitary down-regulation with a GnRH agonist before stimulation with recombinant FSH. Efficacy was assessed using the mean number of fertilized oocytes the day after insemination. The initial doses of GONAL-f® RFF were 150 International Units per day for women less than 35 years of age and 225 International Units per day for women 35 years of age and older. The maximum dose given for both age groups was 450 International Units per day. Treatment outcomes for GONAL-f® RFF are summarized in Table 5.

Table 5: Treatment Outcomes in ART
Study Outcome | value (n)
Mean number of 2PN oocytes per woman | 6.3 (237) [Non-inferior to comparator recombinant human FSH based on a two-sided 95% confidence interval, intent-to-treat analysis.]
Mean number of 2PN oocytes per subject receiving IVF | 6.1 (88) [Subgroup analyses. The study was not powered to demonstrate differences in subgroups.]
Mean number of 2PN oocytes per subject receiving ICSI | 6.5 (132)
Clinical pregnancy [A clinical pregnancy was defined as a pregnancy during which a fetal sac (with or without heart activity) was visualized by ultrasound on day 35-42 after hCG administration.] rate per attempt | 33.5% (218) [Secondary efficacy outcomes. The study was not powered to demonstrate differences in these outcomes.]
Clinical pregnancy rate per embryo transfer | 35.8% (204)
Mean treatment duration in days (range) | 9.7 [3-21] (230)

16 HOW SUPPLIED/STORAGE AND HANDLING

16.1 How Supplied

GONAL-f® RFF Redi-ject® (follitropin alfa) injection is a disposable, prefilled single-patient-use pen containing a clear and colorless to slightly yellow solution. Each Redi-ject® is supplied in a carton containing 31G × 5/16 inch disposable needles to be used for administration.

The following package presentations are available:

NDC 44087-1115-1 - One GONAL-f® RFF Redi-ject® delivers 300 International Units per 0.48 mL and 5 single-use disposable 31G × 5/16" needles

NDC 44087-1116-1 - One GONAL-f® RFF Redi-ject® delivers 450 International Units per 0.72 mL and 7 single-use disposable 31G × 5/16" needles

NDC 44087-1117-1 - One GONAL-f® RFF Redi-ject® delivers 900 International Units per 1.44 mL and 14 single-use disposable 31G × 5/16" needles

16.2 Storage and Handling

Pharmacy Storage: Refrigerate at 2°C to 8°C (36°F to 46°F) until dispensed.

Patient Storage: Refrigerate at 2°C to 8°C (36°F to 46°F) until the expiration date, or store at room temperature at 20° to 25°C (68°F to 77°F) for up to three months or until the expiration date, whichever occurs first. Store pen in the original carton to protect from light. After the first injection, store refrigerated at 2°C to 8°C (36°F to 46°F) or at room temperature at 20°C to 25°C (68°F to 77°F) for up to 28 days. Keep the cap on the pen to protect from light. Do not freeze. Discard unused material after 28 days.

17 PATIENT COUNSELING INFORMATION

See FDA-approved patient labeling (Patient Information and Instructions for Use)

17.1 Dosing and Use of GONAL-f® RFF Redi-ject®

Instruct women on the correct usage and dosing of GONAL-f® RFF Redi-ject® [see Dosage and Administration (2.2, 2.3)]. Instruct women to view the dose display in bright light and to adjust the position of the GONAL-f® RFF Redi-ject® to minimize dose window glare. Caution women not to change the dosage or the schedule of administration unless she is told to do so by her healthcare provider. Instruct women to remove the GONAL-f® RFF Redi-ject® from the refrigerator at least 30 minutes prior to use in order to allow GONAL-f® RFF Redi-ject® to warm to room temperature and avoid the discomfort of a cold injection.

17.2 Duration and Necessary Monitoring in Women Undergoing Therapy with GONAL-f® RFF Redi-ject®

Prior to beginning therapy with GONAL-f® RFF Redi-ject®, inform women about the time commitment and monitoring procedures necessary for treatment [see Dosage and Administration (2.2, 2.3) and Warnings and Precautions (5.11)].

17.3 Instructions Regarding a Missed Dose

Inform the woman that if she misses or forgets to take a dose of GONAL-f® RFF Redi-ject®, the next dose should not be doubled and she should call her healthcare provider for further dosing instructions.

17.4 Ovarian Hyperstimulation Syndrome

Inform women regarding the risks of OHSS [see Warnings and Precautions (5.3)] and OHSS-associated symptoms including lung and blood vessel problems [see Warnings and Precautions (5.4)] and ovarian torsion [see Warnings and Precautions (5.5)] with the use of GONAL-f® RFF Redi-ject®.

17.5 Multi-fetal Gestation and Birth

Inform women regarding the risk of multi-fetal gestation and birth with the use of GONAL-f® RFF Redi-ject® [see Warnings and Precautions (5.6)]

Manufactured by: EMD Serono, Inc., Boston, MA 02210 U.S.A.
U.S. License number: 1773

PATIENT INFORMATION
GONAL-f® RFF Redi-ject® (gon-AL-eff ar-eff-eff REH dee-jekt)
(follitropin alfa)
injection, for subcutaneous use

GONAL-f RFF* Redi-ject (follitropin alfa) injection for subcutaneous use
Read this Patient Information before you start using GONAL-f RFF Redi-ject and each time you get a prescription refill. There may be new information. This information does not take the place of talking to your healthcare provider about your medical condition or your treatment.

What is GONAL-f RFF Redi-ject?
GONAL-f RFF Redi-ject is an injection Pen that delivers a prescription medicine containing follicle-stimulating hormone (FSH) used in infertile women to:

- help healthy ovaries develop (mature) and release an egg
- cause your ovaries to make multiple (more than 1) eggs as part of an Assisted Reproductive Technology (ART) program

Who should not use GONAL-f RFF Redi-ject? Do not use the GONAL-f RFF Redi-ject if you:

- are allergic to recombinant human FSH or any of the ingredients in GONAL-f RFF Redi-ject. See the end of this leaflet for a complete list of ingredients in GONAL-f RFF Redi-ject.
- have a high level of FSH in your blood that shows your ovaries no longer make eggs (primary ovarian failure)
- have uncontrolled thyroid, adrenal, or pituitary problems
- have a tumor in your female organs, including your ovaries, breast, or uterus that may get worse with high levels of estrogen
- have a tumor in your brain, such as a tumor in your pituitary or hypothalamus
- have abnormal bleeding from your uterus or vagina from an unknown cause
- have ovarian cysts or large ovaries from an unknown cause

What should I tell my healthcare provider before using GONAL-f RFF Redi- ject?
Before you use GONAL-f RFF Redi-ject, tell your healthcare provider if you:

- have or have had asthma
- have been told by a healthcare provider that you have an increased risk for blood clots (thrombosis)
- have ever had a blood clot (thrombosis), or anyone in your family has ever had a blood clot (thrombosis)
- have had stomach (abdominal) surgery
- have had twisting of your ovary (ovarian torsion)
- had or have a cyst on your ovary
- have polycystic ovarian disease
- have any other medical conditions
- are pregnant or think you may be pregnant. GONAL-f RFF Redi-ject is not for pregnant women. Your healthcare provider will give you a pregnancy test before starting GONAL-f RFF Redi-ject.
- are breastfeeding. It is not known if GONAL-f RFF Redi-ject passes into your breast milk. You and your healthcare provider should decide if you will take GONAL-f RFF Redi-ject or breastfeed. You should not do both.
- are not an adult. GONAL-f RFF Redi-ject is not for children. It is not known if GONAL-f RFF Redi-ject is safe or works for children.

Tell your healthcare provider about all the medicines you take, including prescription and over-the-counter medicines, vitamins, and herbal supplements.
Know the medicines you take. Keep a list of them to show your healthcare provider and pharmacist when you get a new medicine.

How should I use GONAL-f RFF Redi-ject?

- Read the "Instructions for Use" that comes with GONAL-f RFF Redi-ject for information about the right way to use GONAL-f RFF Redi-ject.
- GONAL-f RFF Redi-ject is given by injection under your skin. Do not inject GONAL-f RFF Redi-ject until your healthcare provider has taught you the correct way to use it.
- Change your injection site as your healthcare provider showed you.
- Use GONAL-f RFF Redi-ject exactly as your healthcare provider tells you to use it.
- Do not change your dose of GONAL-f RFF Redi-ject unless your healthcare provider tells you to.
- Call your healthcare provider if you have any questions about your dose or how to use GONAL-f RFF Redi-ject

What are the possible side effects of GONAL-f RFF Redi-ject
GONAL-f RFF Redi-ject may cause serious side effects, including:

- severe allergic reactions. Women who have used GONAL-f, GONAL-f RFF, or GONAL-f RFF Redi-ject in the past may have a severe allergic reaction right away when they use GONAL-f RFF Redi-ject again. This severe allergic reaction may lead to death. If you have any of the following symptoms of a severe allergic reaction, stop using GONAL-f RFF Redi-ject and go to the hospital right away:
  - shortness of breath
  - swelling of your face
  - itchy, red bumps or rash on your skin (hives)
- ovaries that are too large. GONAL-f RFF Redi-ject may cause your ovaries to be abnormally large. Symptoms of large ovaries include bloating or pain in your lower stomach (pelvic) area.
- ovarian hyperstimulation syndrome (OHSS). Using GONAL-f RFF Redi- ject may cause OHSS. OHSS is a serious medical condition that can happen when your ovaries produce too many eggs (overstimulated). OHSS can cause fluid to suddenly build up in the area of your stomach, chest, and heart, and can cause blood clots to form. In rare cases OHSS has caused death. OHSS may also happen after you stop using GONAL-f RFF Redi-ject. Stop using GONAL-f RFF Redi-ject and call your healthcare provider right away if you have symptoms of OHSS, including:
  - trouble breathing
  - severe lower stomach (pelvic) area pain
  - decreased urine output
  - nausea
  - vomiting
  - weight gain
  - diarrhea
- lung problems. GONAL-f RFF Redi-ject may cause serious lung problems including fluid in your lungs (atelectasis), trouble breathing (acute respiratory distress syndrome), and worsening of asthma.
- blood clots. GONAL-f RFF Redi-ject may increase your chance of having blood clots in your blood vessels. Blood clots can cause:
  - blood vessel problems (thrombophlebitis)
  - stroke
  - loss of your arm or leg
  - blood clot in your lung (pulmonary embolus)
- twisting (torsion) of your ovary. GONAL-f RFF Redi-ject may increase the chance of your ovary twisting if you already have certain conditions such as OHSS, pregnancy and previous abdominal surgery. Twisting of your ovary may lead to blood flow being cut off to your ovary.
- pregnancy with and birth of multiple babies. GONAL-f RFF Redi-ject may increase your chance of having a pregnancy with more than 1 baby. Having a pregnancy and giving birth to more than 1 baby at a time increases the health risk for you and your babies. Your healthcare provider should tell you about your chances of multiple births.
- birth defects. A baby born after an ART cycle may have an increased chance of having birth defects. Your chances of having a baby with birth defects may increase depending on:
  - your age
  - certain sperm problems
  - your genetic background and that of your partner
  - a pregnancy with more than 1 baby at a time
- ectopic pregnancy (pregnancy outside your womb). GONAL-f RFF Redi-ject may increase your chance of having a pregnancy that is abnormally outside of your womb. Your chance of having a pregnancy outside of your womb is increased if you also have fallopian tube problems. Call your healthcare provider right away if you have symptoms of an ectopic pregnancy including:
  - stomach or pelvic pain especially on one side
  - shoulder pain
  - neck pain
  - rectal pain
  - nausea and vomiting
- miscarriage. Your chance of loss of an early pregnancy may be increased if you had difficulty becoming pregnant.
- tumors of the ovary. If you have used medicines like GONAL-f RFF Redi- ject more than 1 time to get pregnant, you may have an increased chance of having tumors in your ovary(ies) (including cancer).

The most common side effects of GONAL-f RFF Redi-ject include:

- ovarian cyst
- headache
- OHSS
- stomach pain
- stomach bloating
- gas
- bruising at the injection site
- nausea
- diarrhea

These are not all the possible side effects of GONAL-f RFF Redi-ject. For more information, call your healthcare provider or pharmacist.
Tell your healthcare provider if you have any side effect that bothers you or that does not go away.
Call your healthcare provider for medical advice about side effects. You may report side effects to FDA at 1-800-FDA-1088.

How should I store GONAL-f RFF Redi-ject?

- Before you use GONAL-f RFF Redi-ject for the first time, store your Pen in the original carton to protect from light:
  - in the refrigerator between 36°F to 46°F (2°C to 8°C) until the expiration date, or
  - store your Pen at room temperature between 68°F to 77°F (20°C to 25°C) for up to 3 months or until the expiration date, whichever comes first
- After you use GONAL-f RFF Redi-ject and there is still medicine left, store your Pen in the refrigerator between 36°F to 46°F (2°C to 8°C) or at room temperature between 68°F to 77°F (20°C to 25°C) up to 28 days. Throw away any unused GONAL-f RFF Redi-ject after 28 days.
- Store your GONAL-f RFF Redi-ject with the Pen cap on in a safe place.
- Store GONAL-f RFF Redi-ject away from light.
- Do not freeze GONAL-f RFF Redi-ject.

Keep GONAL-f RFF Redi-ject and all medicines out of the reach of children.

General Information about the safe and effective use of GONAL-f RFF Redi- ject.
Medicines are sometimes prescribed for purposes other than those listed in a Patient Information leaflet. Do not use GONAL-f RFF Redi-ject for a condition for which it was not prescribed. Do not give GONAL-f RFF Redi-ject to other people, even if they have the same condition that you have. It may harm them.
This Patient Information leaflet summarizes the most important patient information about GONAL-f RFF Redi-ject. If you would like more information, talk with your healthcare provider. You can ask your pharmacist or healthcare provider for information about GONAL-f RFF Redi-ject that is written for health professionals.

What are the ingredients in GONAL-f RFF Redi-ject?
Active ingredient: follitropin alfa
Inactive ingredients: dibasic sodium phosphate, m-cresol, methionine, monobasic sodium phosphate, poloxamer, sucrose and Water for Injection. Phosphoric acid and/or sodium hydroxide may be used for pH adjustment.
For more information, go to www.fertilitylifelines.com, or call 1-866-538-7879.
Manufactured by: EMD Serono, Inc. Boston, MA 02210
U.S. License Number:
1773

This Patient Information has been approved by the U.S. Food and Drug Administration

Revised: 03/2025

INSTRUCTIONS FOR USE

GONAL-f® RFF Redi-ject®
(follitropin alfa) injection
for subcutaneous use

GONAL-f® RFF Redi-ject®
(follitropin alfa) injection

Important Information

- Read this Instructions for Use before you start using GONAL-f RFF Redi-ject and each time you get a prescription refill. There may be new information.
- GONAL-f RFF Redi-ject (follitropin alfa) injection is for use under the skin only (subcutaneous).
- Only use GONAL-f RFF Redi-ject if your healthcare provider trains you on how to use it correctly.

Do not reuse needles.

Do not share your pen or needles with anyone, because doing so can cause an infection.

Do not use the GONAL-f RFF Redi-ject if it has been dropped, or if the pen is cracked or damaged. This can cause an injury.

- The pen comes in 3 different IU amounts
  - For the 300 IU pen, the maximum dose you can dial is 300 IU.
  - For both the 450 IU and 900 IU pens, the maximum dose you can dial is 450 IU.
- Use the attached treatment diary to make sure you take the correct dose. Consult your healthcare provider on proper use of your treatment diary.
- You might need to use more than one pen to give today's intended dose. Contact your healthcare provider with any questions.
- The Dose Information Display is used for setting your dose, to confirm a completed dose, and to display the amount remaining to complete your intended dose.

Gather your supplies

▯ Take the carton out of the refrigerator at least 30 minutes before you inject to let it warm to room temperature.

Do not use a microwave or other heating element to warm up the pen.

▯ Prepare a clean, flat surface, such as a table or countertop, in a well-lit area.
▯ Identify a firm, vertical surface, such as the side of your GONAL-f RFF Redi-ject carton or a wall.
▯ Fill in the first 5 columns of the treatment diary. Refer to the treatment diary for sample entries.
▯ You will also need a sharps disposal container, alcohol pads, and a writing utensil (not included).

Step 1 Get ready

▯ Wash your hands with soap and water and dry them well.

Do not shake the pen. If you shake the pen, air bubbles may appear in the medicine.

▯ Remove the pen and a new needle from the carton using your hands.

Do not use any tools (such as a knife, scissors or box cutters) to take the pen out of the carton because they may damage the pen.

▯ Check that the name on the pen says GONAL-f RFF Redi-ject.
▯ Check the expiration date on the pen label.

Do not use an expired pen. Get a new pen from your healthcare provider.

Step 2 Choose and prepare your injection site

Note: Your healthcare provider should show you the injection sites to use around your stomach area.

▯ Select your injection site and wipe the skin with an alcohol pad to clean the site.

Do not blow on or touch the injection site after cleaning.

▯ Choose a different injection site each time you give your injection to reduce redness, irritation, or other skin problems.

Step 3 Attach your needle

▯ Pull off the pen cap.
▯ Make sure the plastic reservoir that holds the medicine is not cracked. Confirm the medicine is clear, colorless, and does not contain particles. If the plastic is cracked or if the liquid is discolored or cloudy, get a new pen from your healthcare provider. This can cause an infection.
▯ Get a new needle. Only use the single-use needles supplied. Re-using needles can cause infection.
▯ Check that the needle's peel-off seal tab is not broken. If it is, get a new needle.

Do not use the needle if it is damaged, expired or if the outer needle cap or peel-off seal tab is damaged or loose. This can lead to an infection. Throw it away in a sharps disposal container and get a new needle.

▯ Peel off the needle seal.
▯ Push the needle on the clear, plastic end of the pen, and twist the needle until you cannot twist it anymore.

Do not attach the needle too tightly, the needle could be difficult to remove after the injection.

▯ Pull off the outer needle cap and save it for removing the needle after the injection.
▯ Keeping the needle pointing up, carefully pull off the inner needle shield and throw it away.

Do not recap the needle with the inner needle shield, or you could get a needle stick injury.

Important
If | Then
Using a new pen | Check for a droplet of liquid at the tip of the needle.
 | - If you see a droplet go to Step 4 Dial your dose.
 | - If no droplet is seen, or you are unsure, follow the instructions in Appendix B.
Re-using a pen | You do not have to check for droplets of liquid at the tip of the needle. Go to Step 4 Dial your dose.

Step 4 Dial your dose

Note: Call your healthcare provider if you are unsure of today's intended dose.

Do not push or pull the dose knob while you turn it to avoid damaging it.

▯ Turn the dose knob until your intended dose shows in the Dose Information Display.

Note: You can turn the dose knob backward if you turn it past your intended dose.

Step 5 Inject your dose

Important

▯ Make sure the Dose Information Display matches the intended dose recorded in Column 5 in your treatment diary.

Example: If your intended dose is 150 IU, confirm that the Dose Information Display reads "150".

▯ Hold the pen at a 90° angle to the injection site, and push the needle into your skin.

You might bend the needle if you do not insert the needle straight in at a 90° angle.

▯ Place your thumb in the middle of the dose knob. Use your thumb to slowly press the dose knob straight down as far as it will go.

Do not release the dose knob until you remove the needle from your skin. Hold the dose knob down for a slow count of 5 before you remove the needle from your skin. Then release the dose knob after removal of the needle from your skin.

▯ Remove the needle from your skin, release the dose knob, and put the pen on the table.
▯ After injecting, fill in "Yes" or "No" in Column 6 of the treatment diary, to record if the Dose Information Display shows "0".

If the Dose Information Display does not show "0", you did not complete your dose.

- Fill in Column 7 of the treatment diary with the number in the Dose Information Display.
- You will need to use a second pen to inject the number shown in the Dose Information Display to complete your dose.

Step 6 Remove and throw away your needle

You must remove the needle from the pen and throw it away after each injection to avoid risk of infection.

▯ Lay the outer needle cap on its side on a flat surface.
▯ Hold the pen with the needle attached in one hand, and slip the needle into the outer needle cap without using your other hand.
▯ Push the capped needle against a firm, vertical surface, such as a GONAL-f RFF Redi-ject carton or a wall, until you hear a "click".
▯ Twist off the capped needle and throw it away in a FDA-cleared sharps disposal container. See Appendix C for proper disposal information.

▯ After removing the needle, recap the pen.

▯ If the pen is empty after your injection, throw it away in a FDA-cleared sharps disposal container. See Appendix C for proper disposal information.

Step 7 Record your injection

Important

▯ After injecting, fill in Column 7 of the treatment diary by recording the number you see in the Dose Information Display.
▯ If the Dose Information Display shows "0", you have completed your dose.
▯ If the Dose Information Display does not show "0", you did not complete your dose. You need to inject the number shown in the Dose Information Display using a second pen.
  - Follow the instructions in Appendix A: Completing an incomplete dose.
  - The amount you need to inject using the second pen might be less than expected because of the extra medicine (see note below). Always inject the amount you wrote in Column 7 of the treatment diary to complete your dose.
  - Refer to the treatment diary for sample entries.

Note: The pen contains extra medicine to ensure that you receive the full amount indicated on the pen (300 IU, 450 IU, or 900 IU).

Appendix A: Completing an incomplete dose

▯ The number recorded in Column 7 in the treatment diary indicates the number you need to dial with the second pen to complete today's intended dose. To complete the dose with a second pen, repeat Steps 1 through 7.

Appendix B: How to create a droplet of liquid

▯ If you do not see a droplet of liquid on the tip of the needle when using a pen for the first time, turn the dose knob until the Dose Information Display reads "25".
▯ With the needle pointing up, gently tap the reservoir so that any air bubbles rise to the top.
▯ Hold the pen with the needle pointing up. Slowly press the dose knob in all the way. One or more tiny drops of liquid will appear at the tip of the needle. Release the dose knob. Make sure that the Dose Information Display reads "0".
▯ Go to Step 4 Dial your dose.
▯ If a droplet of liquid does not appear, contact your healthcare provider.

Appendix C: How to throw away used needles and empty pens

▯ Put used needles and empty pens in a FDA-cleared sharps disposal container immediately after use.

Do not throw away loose needles and pens in your household trash.

▯ If you do not have a FDA-cleared sharps disposal container, you may use a household container that is:
  - Made of heavy-duty plastic,
  - Can be closed with a tight-fitting, puncture-resistant lid, without sharps being able to come out,
  - Upright and stable during use,
  - Leak-resistant, and
  - Properly labeled to warn of hazardous waste inside the container.
▯ When your sharps disposal container is almost full, you will need to follow your community guidelines for the right way to dispose of your sharps disposal container. There may be state or local laws about how you should throw away used needles and syringes. For more information about safe sharps disposal, and for specific information about sharps disposal in the state that you live in, go to the FDA's website at: http://www.fda.gov/safesharpsdisposal.
  - Do not reuse the needles.
  - Do not throw away (dispose of) your used sharps disposal container in your household trash unless your community guidelines permit this.
  - Do not recycle your used sharps disposal container.
  For more information, go to http:/www.fda.gov/safesharpsdisposal.

Appendix D: How to store your pen

▯ Store all pens with the cap attached and away from light.
▯ Store new pens in the refrigerator between 36°F and 46°F (2°C and 8°C) until the expiration date, or at room temperature between 68°F and 77°F (20°C and 25°C) for up to 3 months or until the expiration date, whichever comes first. Store pen in the original carton to protect from light.
▯ Do not freeze the pen.
▯ Keep the pen out of reach of children.
▯ If you have medicine left in a pen after injecting, store it in the refrigerator or at room temperature for up to 28 days. After 28 days, you must throw away your pen in a FDA-cleared sharps disposal container. See Appendix C for proper disposal information.

For more information, call 1-866-538-7879.

To view the Instructions for Use video, please visit www.Rediject.com.

EMD Serono, Inc

Boston, MA 02210

US License number: 1773

This Instructions for Use has been approved by the U.S. Food and Drug Administration.

Revised: 03/2025

PRINCIPAL DISPLAY PANEL - 300 IU/0.48 mL Package Carton

NDC 44087-1115-1

GONAL-f® RFF Redi-ject® 300 IU/0.48 mL

(follitropin alfa) injection

For subcutaneous injection
Do not shake
Rx only

1 Gonal-f® RFF Redi-ject®
5 needles for injection (31 gauge)

EMD
SERONO

PRINCIPAL DISPLAY PANEL - 450 IU/0.72 mL Package Carton

NDC 44087-1116-1

GONAL-f® RFF Redi-ject® 450 IU/0.72 mL

(follitropin alfa) injection

For subcutaneous injection
Do not shake
Rx only

1 Gonal-f® RFF Redi-ject®
7 needles for injection (31 gauge)

EMD
SERONO

PRINCIPAL DISPLAY PANEL - 900 IU/1.44 mL Package Carton

NDC 44087-1117-1

GONAL-f® RFF Redi-ject® 900 IU/1.44 mL

(follitropin alfa) injection

For subcutaneous injection
Do not shake
Rx only

1 Gonal-f® RFF Redi-ject®
14 needles for injection (31 gauge)

EMD
SERONO